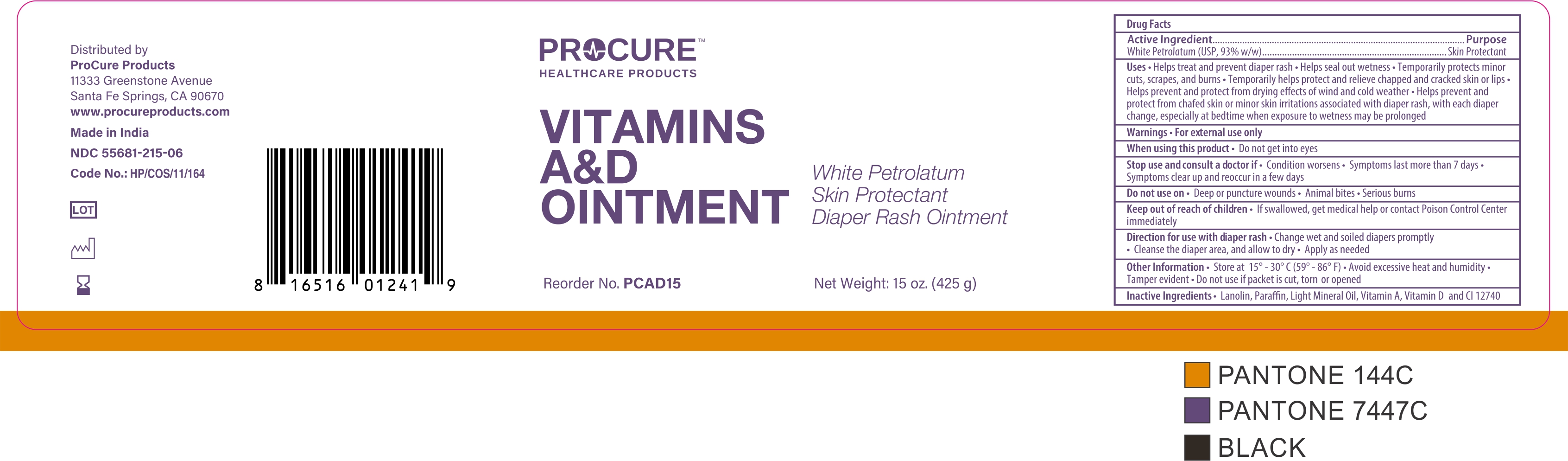 DRUG LABEL: PROCURE VITAMIN A AND D

NDC: 55681-215 | Form: OINTMENT
Manufacturer: TWIN MED, LLC
Category: otc | Type: HUMAN OTC DRUG LABEL
Date: 20250611

ACTIVE INGREDIENTS: PETROLATUM 93.4 g/100 g
INACTIVE INGREDIENTS: SOLVENT YELLOW 18; LANOLIN; LIGHT MINERAL OIL; VITAMIN A; VITAMIN D

Drug Facts

Active Ingredients(in each gram)

White Petrolatum (USP 93.4% w/w)

Purpose

Skin Protectant

Uses

- Helps treat and prevent diaper rash
- Helps seal out wetness
- Temporarily protects minor cuts, scrapes and burns
- Temporarily helps protect and helps relieve chapped and cracked skin or lips
- Helps prevent and protect from the drying effects of wind and cold weather
- Helps prevent and protect chafed skin or minor skin irritations associated with diaper rash, with each diaper change, especially at bedtime when exposure to wet diapers may be prolonged

Warnings

For External Use Only.

When using this product

- Avoid contact with eyes

Stop use and ask doctor if

- The condition persists or get worse
- Symptoms last more than 7 days or clear up and occur again in a few days

Do not use on

- Deep or puncture wounds
- Animal bites
- Serious burns

Keep out of reach of children

- If swallowed, get medical help or contact a Poison Control Center right away

Directions

- Change wet and soiled diapers promptly
- Cleanse the diaper area, and allow to dry
- Apply as needed

Other Information

- Store at room temperature 150 - 300 c (590 - 860 F)
- Avoid excessive heat and humidity
- Tamper Evident
- Do not use if packet it torn, cut or opened.

Inactive Ingredients

CI 17240, Lanolin, Light Liquid Paraffin, Vitamin A, Vitamin D